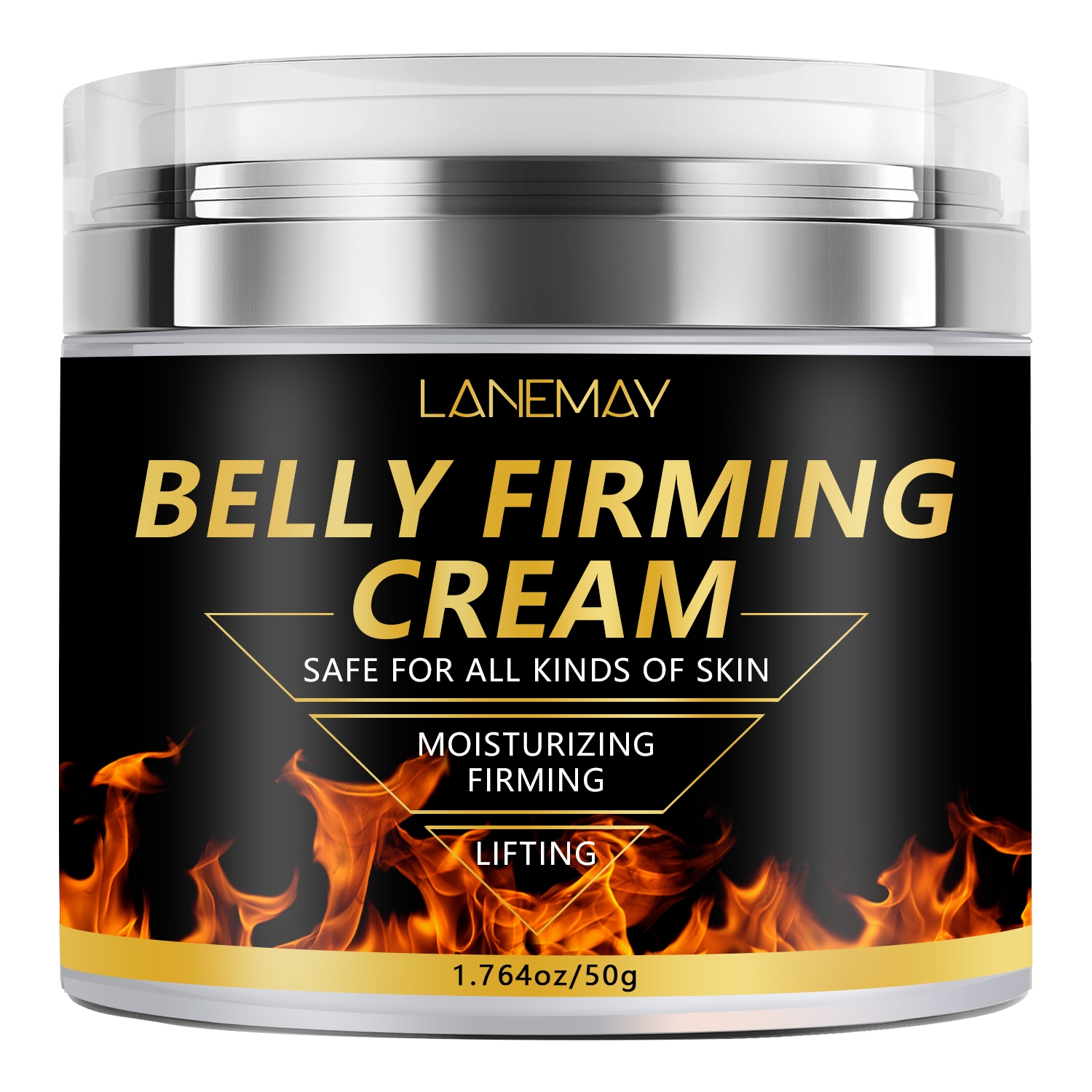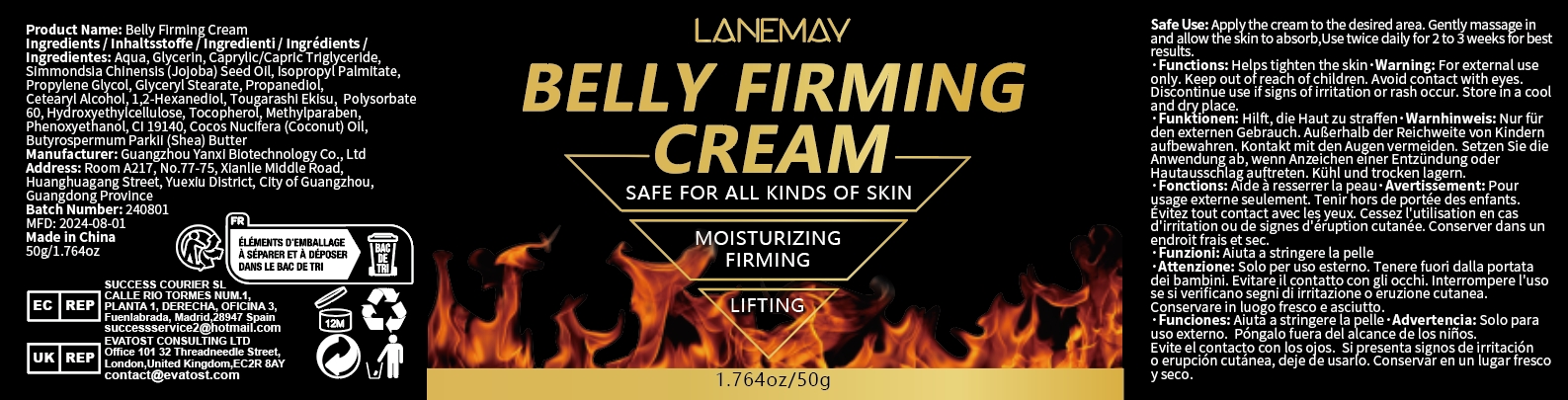 DRUG LABEL: Belly Firming Cream
NDC: 84025-240 | Form: CREAM
Manufacturer: Guangzhou Yanxi Biotechnology Co., Ltd
Category: otc | Type: HUMAN OTC DRUG LABEL
Date: 20241028

ACTIVE INGREDIENTS: CAPRYLIC/CAPRIC TRIGLYCERIDE 2 mg/50 g; GLYCERIN 3 mg/50 g
INACTIVE INGREDIENTS: WATER

DOSAGE AND ADMINISTRATION

Apply the cream to the desired area.Gently massage in and allow the skin to absorb,Use twice daily for 2to 3weeks for best results.

WARNINGS

Keep out of children

INACTIVE INGREDIENT

Aqua

INDICATIONS AND USAGE

For daily skin care

Keep out of children

PURPOSE

Moisturizing and firming the skin